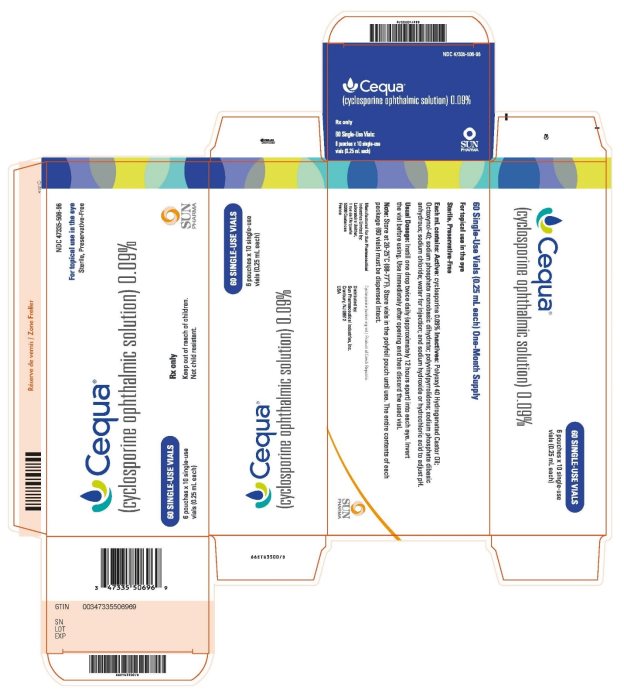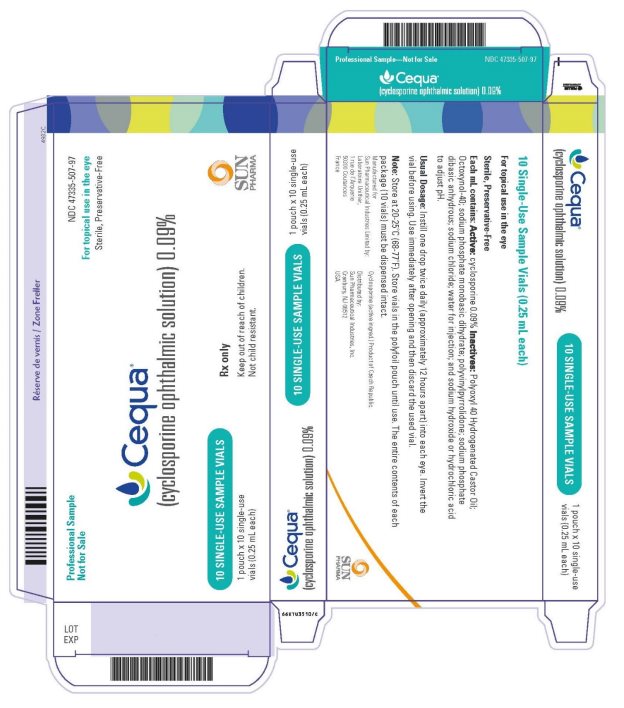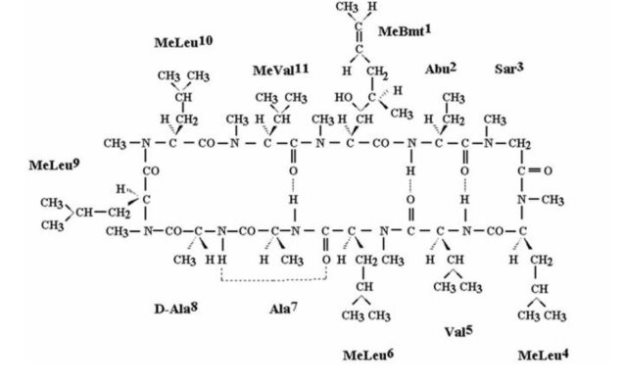 DRUG LABEL: CEQUA
NDC: 47335-506 | Form: SOLUTION/ DROPS
Manufacturer: Sun Pharmaceutical Industries, Inc.
Category: prescription | Type: HUMAN PRESCRIPTION DRUG LABEL
Date: 20250306

ACTIVE INGREDIENTS: CYCLOSPORINE 0.0009 g/1 mL
INACTIVE INGREDIENTS: POLYOXYL 40 HYDROGENATED CASTOR OIL 0.01 g/1 mL; OCTOXYNOL-40 0.0005 g/1 mL; SODIUM PHOSPHATE, MONOBASIC, DIHYDRATE 0.0053 g/1 mL; SODIUM PHOSPHATE, DIBASIC, ANHYDROUS 0.0047 g/1 mL; SODIUM CHLORIDE 0.0005 g/1 mL; POVIDONE K90 0.003 g/1 mL; HYDROCHLORIC ACID; SODIUM HYDROXIDE; WATER

HIGHLIGHTS OF PRESCRIBING INFORMATION

These highlights do not include all the information needed to use CEQUA safely and effectively. See full prescribing information for CEQUA.
CEQUA® (cyclosporine ophthalmic solution) 0.09%, for topical ophthalmic use
Initial U.S. Approval: 1983

1 INDICATIONS AND USAGE

CEQUA ophthalmic solution is a calcineurin inhibitor immunosuppressant indicated to increase tear production in patients with keratoconjunctivitis sicca (dry eye) (1).

2 DOSAGE AND ADMINISTRATION

Instill one drop of CEQUA twice daily (approximately 12 hours apart) into each eye. Discard the vial immediately after using in both eyes (2).

3 DOSAGE FORMS AND STRENGTHS

Ophthalmic solution containing cyclosporine 0.9 mg/mL (3).

4 CONTRAINDICATIONS

None (4).

5 WARNINGS AND PRECAUTIONS

To avoid the potential for eye injury and contamination, advise patients not to touch the vial tip to the eye or other surfaces (5.1).

6 ADVERSE REACTIONS

The most common adverse reactions following the use of CEQUA (cyclosporine ophthalmic solution) 0.09% was instillation site pain (22%) and conjunctival hyperemia (6%) (6.1).

To report SUSPECTED ADVERSE REACTIONS, contact Sun Pharmaceutical Industries, Inc. at 1-800-406-7984 or FDA at 1-800-FDA-1088 or www.fda.gov/medwatch.

FULL PRESCRIBING INFORMATION

1 INDICATIONS AND USAGE

CEQUA ophthalmic solution is a calcineurin inhibitor immunosuppressant indicated to increase tear production in patients with keratoconjunctivitis sicca (dry eye). (1)

2 DOSAGE AND ADMINISTRATION

Instill one drop of CEQUA twice daily (approximately 12 hours apart) into each eye. CEQUA can be used concomitantly with artificial tears, allowing a 15 minute interval between products. Discard the vial immediately after using in both eyes. (2)

3 DOSAGE FORMS AND STRENGTHS

Ophthalmic solution containing cyclosporine 0.9 mg/mL (3)

4 CONTRAINDICATIONS

None. (4)

5 WARNINGS AND PRECAUTIONS

5.1 Potential for Eye Injury and Contamination

To avoid the potential for eye injury and contamination, advise patients not to touch the vial tip to the eye or other surfaces.

5.2 Use with Contact Lenses

CEQUA should not be administered while wearing contact lenses. If contact lenses are worn, they should be removed prior to administration of the solution. Lenses may be reinserted 15 minutes following administration of CEQUA ophthalmic solution.

6 ADVERSE REACTIONS

6.1 Clinical Trials Experience

Because clinical trials are conducted under widely varying conditions, adverse reaction rates observed in the clinical trials of a drug cannot be directly compared to rates in the clinical trials of another drug and may not reflect the rates observed in practice.

In clinical trials, 769 subjects received at least 1 dose of cyclosporine ophthalmic solution. The majority of the treated subjects were female (83%). The most common adverse reactions reported in greater than 5% of subjects were pain on instillation of drops (22%) and conjunctival hyperemia (6%). Other adverse reactions reported in 1% to 5% of the patients were blepharitis, eye irritation, headache, and urinary tract infection.

8 USE IN SPECIFIC POPULATIONS

8.1 Pregnancy

Risk Summary

There are no adequate and well-controlled studies of CEQUA administration in pregnant women to inform a drug-associated risk. Oral administration of cyclosporine to pregnant rats or rabbits did not produce teratogenicity at clinically relevant doses [see Data].

Data

Animal Data

Oral administration of cyclosporine oral solution (USP) to pregnant rats or rabbits was teratogenic at maternally toxic doses of 30 mg/kg/day in rats and 100 mg/kg/day in rabbits, as indicated by increased pre- and postnatal mortality, reduced fetal weight and skeletal retardations. These doses (normalized to body weight) were approximately 3200 and 21000 times higher than the maximum recommended human ophthalmic dose (MRHOD) of 1.5 mcg/kg/day, respectively. No adverse embryofetal effects were observed in rats or rabbits receiving cyclosporine during organogenesis at oral doses up to 17 mg/kg/day or 30 mg/kg/day, respectively (approximately 1800 and 6400 times higher than the MRHOD, respectively).

An oral dose of 45 mg/kg/day cyclosporine (approximately 4800 times higher than MRHOD) administered to rats from Day 15 of pregnancy until Day 21 postpartum produced maternal toxicity and an increase in postnatal mortality in offspring. No adverse effects in dams or offspring were observed at oral doses up to 15 mg/kg/day (approximately 1600 times greater than the MRHOD).

8.2 Lactation

Risk Summary

Cyclosporine blood concentrations are low following topical ocular administration of CEQUA [see Clinical Pharmacology (12.3)]. There is no information regarding the presence of cyclosporine in human milk following topical administration or on the effects of CEQUA on the breastfed infants and milk production. Administration of oral cyclosporine to rats during lactation did not produce adverse effects in offspring at clinically relevant doses [see Pregnancy (8.1)]. The developmental and health benefits of breastfeeding should be considered along with the mother’s clinical need for CEQUA and any potential adverse effects on the breast-fed child from cyclosporine.

8.4 Pediatric Use

The safety and efficacy of CEQUA ophthalmic solution have not been established in pediatric patients below the age of 18.

8.5 Geriatric Use

No overall differences in safety or effectiveness have been observed between elderly and younger adult patients.

11 DESCRIPTION

CEQUA (cyclosporine ophthalmic solution) 0.09% contains a topical calcineurin inhibitor immunosuppressant. Cyclosporine’s chemical name is Cyclo[[(E)-(2S,3R,4R)-3-hydroxy-4-methyl-2-(methylamino)-6-octenoyl]-L-2-aminobutyryl-N-methylglycyl-N-methyl-L-leucyl-L-valyl-N-methyl-L-leucyl-L-alanyl-D-alanyl-N-methyl-L-leucyl-N-methyl-L-leucyl-N-methyl-L-valyl] and it has the following structure:

Structural Formula

Formula: C62H111N11O12 Mol. Wt.: 1202.6

Cyclosporine is a white powder that is insoluble in water. CEQUA is supplied as a sterile, clear, colorless ophthalmic solution for topical ophthalmic use. It has an osmolality of 160 to 190 mOsmol/kg and a pH of 6.5-7.2. Each mL of CEQUA contains:

- Active: cyclosporine 0.09%
- Inactives: Polyoxyl 40 Hydrogenated Castor Oil, Octoxynol-40, polyvinylpyrrolidone, sodium phosphate monobasic dihydrate, sodium phosphate dibasic anhydrous, sodium chloride, water for injection, and sodium hydroxide or hydrochloric acid to adjust pH.

12 CLINICAL PHARMACOLOGY

12.1 Mechanism of Action

Cyclosporine is a calcineurin inhibitor immunosuppressant agent when administered systemically. In patients whose tear production is presumed to be suppressed due to ocular inflammation associated with keratoconjunctivitis sicca, topical administration of cyclosporine is thought to act as a partial immunomodulator. The exact mechanism of action is not known.

12.3 Pharmacokinetics

Blood concentrations of cyclosporine after twice daily topical ocular administration of CEQUA into each eye of healthy subjects for up to 7 days, and once on Day 8, were either not detectable or were marginally above the lower limit of assay quantitation of 0.100 ng/mL (range 0.101 to 0.195 ng/mL) for up to 2 hours after a single dose, and up to 4 hours after multiple doses.

13 NONCLINICAL TOXICOLOGY

13.1 Carcinogenesis, Mutagenesis, Impairment of Fertility

Carcinogenesis

Systemic carcinogenicity studies were carried out in male and female mice and rats. In the 78-week oral (diet) mouse study, at doses of 1, 4, and 16 mg/kg/day, evidence of a statistically significant trend was found for lymphocytic lymphomas in females, and the incidence of hepatocellular carcinomas in mid-dose males significantly exceeded the control value.

In the 24-month oral (diet) rat study, conducted at 0.5, 2, and 8 mg/kg/day, pancreatic islet cell adenomas significantly exceeded the control rate in the low dose level. The hepatocellular carcinomas and pancreatic islet cell adenomas were not dose related. The low doses in mice and rats are approximately 55 times higher than the maximum recommended human ophthalmic dose (1.5 mcg/kg/day), normalized to body surface area.

Mutagenesis

In genetic toxicity tests, cyclosporine has not been found to be mutagenic/genotoxic in the Ames Test, the V79-HGPRT Test, the micronucleus test in mice and Chinese hamsters, the chromosome-aberration tests in Chinese hamster bone-marrow, the mouse dominant lethal assay, and the DNA-repair test in sperm from treated mice. Cyclosporine was positive in an in vitro sister chromatid exchange (SCE) assay using human lymphocytes.

Impairment of Fertility

Oral administration of cyclosporine to rats for 12 weeks (male) and 2 weeks (female) prior to mating produced no adverse effects on fertility at doses up to 15 mg/kg/day (1620 times higher than the maximum recommended human ophthalmic dose).

14 CLINICAL STUDIES

Two multicenter, randomized, adequate and well-controlled clinical studies treated 1,048 patients with keratoconjunctivitis sicca (NCT # 02254265 and NCT # 02688556). In both studies, compared to vehicle at Day 84, there was a statistically significant (p<0.01) higher percentage of eyes with increases of ≥ 10 mm from baseline in Schirmer wetting. This effect was seen in approximately 17% of CEQUA-treated patients versus approximately 9% of vehicle-treated patients.

Tear Production
 | OTX-101-2014-001 |  | OTX-101-2016-001
 | CEQUA; N=152 | Vehicle; N=152 | CEQUA; N=371 | Vehicle; N=373
≥ 10-mm increase in tear production; (% of eyes) at Day 84 | 16.8% | 8.6% | 16.6% | 9.2%
Difference (95% CI) | 8.2% (1.9%, 14.6%) |  | 7.3% (3.3%, 11.3%)
p-value versus vehicle | <0.01 |  | <0.01

16 HOW SUPPLIED/STORAGE AND HANDLING

CEQUA ophthalmic solution is packaged in sterile, preservative-free, single-use vials. Each vial

contains 0.25 mL fill in a 0.9 mL LDPE vial; 10 vials (2 cards of 5 vials) are packaged in a

polyfoil aluminum pouch; 6 pouches are packaged in a box. The entire contents of each box of

60 vials must be dispensed intact.

60 Single-Use Vials 0.25 mL each - NDC 47335-506-96

Storage: Store at 20°C to 25°C (68°F to 77°F). Store single-use vials in the original foil pouch.

17 PATIENT COUNSELING INFORMATION

Handling the Vial

Advise patients to not allow the tip of the vial to touch the eye or any surface, as this may

contaminate the solution. Advise patients also not to touch the vial tip to their eye to avoid the

potential for injury to the eye [see Warnings and Precautions (5.1)].

Use with Contact Lenses

CEQUA should not be administered while wearing contact lenses. Patients with decreased tear

production typically should not wear contact lenses. Advise patients that if contact lenses are

worn, they should be removed prior to the administration of the solution. Lenses may be

reinserted 15 minutes following administration of CEQUA ophthalmic solution [see Warnings

and Precautions (5.2)].

Administration

Advise patients that the solution from one individual single-use vial is to be used immediately

after opening for administration to one or both eyes, and the remaining contents should be

discarded immediately after administration.

Rx Only

Manufactured for: Sun Pharmaceutical Industries Limited

By: Laboratoire Unither

1 rue de l’Arquerie

50200 Coutances

France

Cyclosporine (active ingred.) Product of Czech Republic.

Product of France

Distributed by:

Sun Pharmaceutical Industries, Inc.

Cranbury, NJ 08512

Copyright 2022, Sun Pharmaceutical Industries Limited

All rights reserved

07/2022

uspi-CEQUA-sol-00004

PACKAGE LABEL

PRINCIPAL DISPLAY PANEL

NDC 47355-506-96

For topical use in the eye
sterile, Preservative-Free

Cequa®
(cyclosporine ophthalmic solution) 0.09%

60 SINGLE-USE VIALS

6 pouches x 10 single-use vials (0.25 mL each)

Rx only

Keep out of reach of children.
Not child resistant.

SUN PHARMA

PACKAGE LABEL

PRINCIPAL DISPLAY PANEL

NDC 47355-507-97

For topical use in the eye
sterile, Preservative-Free

Cequa®
(cyclosporine ophthalmic solution) 0.09%

10 SINGLE-USE SAMPLE VIALS

1 pouches x 10 single-use vials (0.25 mL each)

Rx only

Keep out of reach of children.
Not child resistant.

SUN PHARMA